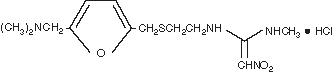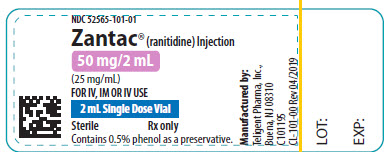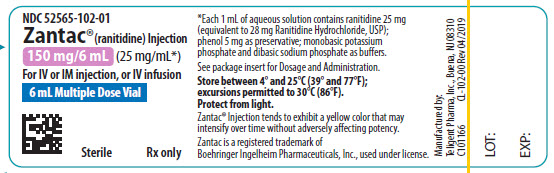 DRUG LABEL: ZANTAC
NDC: 52565-101 | Form: INJECTION, SOLUTION
Manufacturer: Teligent Pharma, Inc.
Category: prescription | Type: HUMAN PRESCRIPTION DRUG LABEL
Date: 20200521

ACTIVE INGREDIENTS: RANITIDINE HYDROCHLORIDE 25 mg/1 mL
INACTIVE INGREDIENTS: PHENOL; POTASSIUM PHOSPHATE, MONOBASIC; SODIUM PHOSPHATE, DIBASIC

ZANTAC® (ranitidine) Injection
Rx only

DESCRIPTION

The active ingredient in ZANTAC Injection is ranitidine hydrochloride (HCl), a histamine H2-receptor antagonist. Chemically it is N[2-[[[5-[(dimethylamino)methyl]-2-furanyl]methyl]thio]ethyl]-N′-methyl-2-nitro-1,1-ethenediamine, hydrochloride. It has the following structure:

The empirical formula is C13H22N4O3S●HCl, representing a molecular weight of 350.87.

Ranitidine HCl is a white to pale yellow, granular substance that is soluble in water.

ZANTAC® Injection is a clear, colorless to yellow, nonpyrogenic liquid. The yellow color of the liquid tends to intensify without adversely affecting potency. The pH of the injection solution is 6.7 to 7.3.

Sterile Injection for Intramuscular or Intravenous Administration

Each 1 mL of aqueous solution contains ranitidine 25 mg (equivalent to 28 mg ranitidine hydrochloride, USP); phenol 5 mg as preservative; and 0.96 mg of monobasic potassium phosphate and 2.4 mg of dibasic sodium phosphate as buffers.

CLINICAL PHARMACOLOGY

ZANTAC is a competitive, reversible inhibitor of the action of histamine at the histamine H2-receptors, including receptors on the gastric cells. ZANTAC does not lower serum Ca++ in hypercalcemic states. ZANTAC is not an anticholinergic agent.

Pharmacokinetics

Absorption: ZANTAC is absorbed very rapidly after intramuscular (IM) injection. Mean peak levels of 576 ng/mL occur within 15 minutes or less following a 50-mg IM dose. Absorption from IM sites is virtually complete, with a bioavailability of 90% to 100% compared with intravenous (IV) administration. Following oral administration, the bioavailability of ZANTAC Tablets is 50%.

Distribution: The volume of distribution is about 1.4 L/kg. Serum protein binding averages 15%.

Metabolism: In humans, the N-oxide is the principal metabolite in the urine; however, this amounts to <4% of the dose. Other metabolites are the S-oxide (1%) and the desmethyl ranitidine (1%). The remainder of the administered dose is found in the stool. Studies in patients with hepatic dysfunction (compensated cirrhosis) indicate that there are minor, but clinically insignificant, alterations in ranitidine half-life, distribution, clearance, and bioavailability.

Excretion: Following IV injection, approximately 70% of the dose is recovered in the urine as unchanged drug. Renal clearance averages 530 mL/min, with a total clearance of 760 mL/min. The elimination half-life is 2.0 to 2.5 hours.

Four patients with clinically significant renal function impairment (creatinine clearance 25 to 35 mL/min) administered 50 mg of ranitidine intravenously had an average plasma half-life of 4.8 hours, a ranitidine clearance of 29 mL/min, and a volume of distribution of 1.76 L/kg. In general, these parameters appear to be altered in proportion to creatinine clearance (see DOSAGE AND ADMINISTRATION).

Geriatrics: The plasma half-life is prolonged and total clearance is reduced in the elderly population due to a decrease in renal function. The elimination half-life is 3.1 hours (see PRECAUTIONS: Geriatric Use and DOSAGE AND ADMINISTRATION: Dosage Adjustment for Patients With Impaired Renal Function).

Pediatrics: There are no significant differences in the pharmacokinetic parameter values for ranitidine in pediatric patients (from 1 month up to 16 years of age) and healthy adults when correction is made for body weight. The pharmacokinetics of ZANTAC in pediatric patients are summarized in Table 1.

Table 1. Ranitidine Pharmacokinetics in Pediatric Patients Following IV Dosing
Population; (age) | n | Dose; (mg/kg) | t½; (hours) | Vd; (L/kg) | CLp; (mL/min/kg)
Peptic ulcer disease; (<6 years); (6 − 11.9 years); (>12 years); Adults | 6; 11; 6; 6 | 1.25 or 2.5; 1.25 or 2.5; 1.25 or 2.5; 2.5 | 2.2; 2.1; 1.7; 1.9 | 1.29; 1.14; 0.98; 1.04 | 11.41; 8.96; 9.89; 8.77
Peptic ulcer disease; (3.5 − 16 years) | 12 | 0.13 − 0.80 | 1.8 | 2.3 | 795 mL/min/1.73/m^2
Children in intensive care; (1 day − 12.6 years) | 17 | 1.0 | 2.4 | 2 | 11.7
Neonates receiving ECMO | 12 | 2 | 6.6 | 1.8 | 4.3

T½= Terminal half-life; CLp = Plasma clearance of ranitidine.

ECMO = extracorporeal membrane oxygenation.

Plasma clearance in neonatal patients (less than 1 month of age) receiving ECMO was considerably lower (3 to 4 mL/min/kg) than observed in children or adults. The elimination half-life in neonates averaged 6.6 hours as compared to approximately 2 hours in adults and pediatric patients.

Pharmacodynamics

Serum concentrations necessary to inhibit 50% of stimulated gastric acid secretion are estimated to be 36 to 94 ng/mL. Following single IV or IM 50-mg doses, serum concentrations of ranitidine are in this range for 6 to 8 hours.

Antisecretory Activity:
1. Effects on Acid Secretion: ZANTAC Injection inhibits basal gastric acid secretion as well as gastric acid secretion stimulated by betazole and pentagastrin, as shown in Table 2.

Table 2. Effect of Intravenous ZANTAC on Gastric Acid Secretion
 | Time After Dose,; hours | % Inhibition of Gastric Acid Output; by Intravenous Dose, mg
 | Time After Dose,; hours | 20 mg | 60 mg | 100 mg
Betazole; Pentagastrin | Up to 2; Up to 3 | 93; 47 | 99; 66 | 99; 77

In a group of 10 known hypersecretors, ranitidine plasma levels of 71, 180, and 376 ng/mL inhibited basal acid secretion by 76%, 90%, and 99.5%, respectively.

It appears that basal- and betazole-stimulated secretions are most sensitive to inhibition by ZANTAC, while pentagastrin-stimulated secretion is more difficult to suppress.

2. Effects on Other Gastrointestinal Secretions:

Pepsin: ZANTAC does not affect pepsin secretion. Total pepsin output is reduced in proportion to the decrease in volume of gastric juice.

Intrinsic Factor: ZANTAC has no significant effect on pentagastrin-stimulated intrinsic factor secretion.

Serum Gastrin: ZANTAC has little or no effect on fasting or postprandial serum gastrin.

Other Pharmacologic Actions:

1. Gastric bacterial flora―increase in nitrate-reducing organisms, significance not known.
2. Prolactin levels―no effect in recommended oral or IV dosage, but small, transient, dose-related increases in serum prolactin have been reported after IV bolus injections of 100 mg or more.
3. Other pituitary hormones―no effect on serum gonadotropins, TSH, or GH. Possible impairment of vasopressin release.
4. No change in cortisol, aldosterone, androgen, or estrogen levels.
5. No antiandrogenic action.
6. No effect on count, motility, or morphology of sperm.

Pediatrics: The ranitidine concentration necessary to suppress basal acid secretion by at least 90% has been reported to be 40 to 60 ng/mL in pediatric patients with duodenal or gastric ulcers.

In a study of 20 critically ill pediatric patients receiving ranitidine IV at 1 mg/kg every 6 hours, 10 patients with a baseline pH≥4 maintained this baseline throughout the study. Eight of the remaining 10 patients with a baseline of pH≤2 achieved pH≥4 throughout varying periods after dosing. It should be noted, however, that because these pharmacodynamic parameters were assessed in critically ill pediatric patients, the data should be interpreted with caution when dosing recommendations are made for a less seriously ill pediatric population.

In another small study of neonatal patients (n = 5) receiving ECMO, gastric pH<4 pretreatment increased to >4 after a 2-mg/kg dose and remained above 4 for at least 15 hours.

Clinical Trials

Active Duodenal Ulcer: In a multicenter, double-blind, controlled, US study of endoscopically diagnosed duodenal ulcers, earlier healing was seen in the patients treated with oral ZANTAC as shown in Table 3.

Table 3. Duodenal Ulcer Patient Healing Rates
 | Oral ZANTAC* |  | Oral Placebo*
 | Number; Entered | Healed/; Evaluable | Number; Entered | Healed/; Evaluable
Outpatients
Week 2 |  | 69/182; (38%)† |  | 31/164; (19%)
 | 195 |  | 188
Week 4 |  | 137/187; (73%)† |  | 76/168; (45%)

*All patients were permitted antacids as needed for relief of pain.

† P<0.0001.

In these studies, patients treated with oral ZANTAC reported a reduction in both daytime and nocturnal pain, and they also consumed less antacid than the placebo-treated patients.

Table 4. Mean Daily Doses of Antacid
 | Ulcer Healed | Ulcer Not Healed
Oral ZANTAC; Oral placebo | 0.06; 0.71 | 0.71; 1.43

Pathological Hypersecretory Conditions (such as Zollinger-Ellison syndrome): ZANTAC inhibits gastric acid secretion and reduces occurrence of diarrhea, anorexia, and pain in patients with pathological hypersecretion associated with Zollinger-Ellison syndrome, systemic mastocytosis, and other pathological hypersecretory conditions (e.g., postoperative, "short-gut" syndrome, idiopathic). Use of oral ZANTAC was followed by healing of ulcers in 8 of 19 (42%) patients who were intractable to previous therapy.

In a retrospective review of 52 Zollinger-Ellison patients given ZANTAC as a continuous IV infusion for up to 15 days, no patients developed complications of acid-peptic disease such as bleeding or perforation. Acid output was controlled to ≤10 mEq/h.

INDICATIONS AND USAGE

ZANTAC Injection is indicated in some hospitalized patients with pathological hypersecretory conditions or intractable duodenal ulcers, or as an alternative to the oral dosage form for short-term use in patients who are unable to take oral medication.

CONTRAINDICATIONS

ZANTAC Injection is contraindicated for patients known to have hypersensitivity to the drug.

PRECAUTIONS

General

1. Symptomatic response to therapy with ZANTAC does not preclude the presence of gastric malignancy.
2. Since ZANTAC is excreted primarily by the kidney, dosage should be adjusted in patients with impaired renal function (see DOSAGE AND ADMINISTRATION). Caution should be observed in patients with hepatic dysfunction since ZANTAC is metabolized in the liver.
3. In controlled studies in normal volunteers, elevations in SGPT have been observed when H2-antagonists have been administered intravenously at greater-than-recommended dosages for 5 days or longer. Therefore, it seems prudent in patients receiving IV ranitidine at dosages ≥100 mg 4 times daily for periods of 5 days or longer to monitor SGPT daily (from day 5) for the remainder of IV therapy.
4. Bradycardia in association with rapid administration of ZANTAC Injection has been reported rarely, usually in patients with factors predisposing to cardiac rhythm disturbances. Recommended rates of administration should not be exceeded (see DOSAGE AND ADMINISTRATION).
5. Rare reports suggest that ZANTAC may precipitate acute porphyric attacks in patients with acute porphyria. ZANTAC should therefore be avoided in patients with a history of acute porphyria.

Laboratory Tests

False-positive tests for urine protein with MULTISTIX® may occur during therapy with ZANTAC, and therefore testing with sulfosalicylic acid is recommended.

Drug Interactions

Ranitidine has been reported to affect the bioavailability of other drugs through several different mechanisms such as competition for renal tubular secretion, alteration of gastric pH, and inhibition of cytochrome P450 enzymes.

Procainamide: Ranitidine, a substrate of the renal organic cation transport system, may affect the clearance of other drugs eliminated by this route. High doses of ranitidine (e.g., such as those used in the treatment of Zollinger-Ellison syndrome) have been shown to reduce the renal excretion of procainamide and N-acetylprocainamide resulting in increased plasma levels of these drugs. Although this interaction is unlikely to be clinically relevant at usual ranitidine doses, it may be prudent to monitor for procainamide toxicity when administered with oral ranitidine at a dose exceeding 300 mg per day.

Warfarin: There have been reports of altered prothrombin time among patients on concomitant warfarin and ranitidine therapy. Due to the narrow therapeutic index, close monitoring of increased or decreased prothrombin time is recommended during concurrent treatment with ranitidine.

Ranitidine may alter the absorption of drugs in which gastric pH is an important determinant of bioavailability. This can result in either an increase in absorption (e.g., triazolam, midazolam, glipizide) or a decrease in absorption (e.g., ketoconazole, atazanavir, delavirdine, gefitinib). Appropriate clinical monitoring is recommended.

Atazanavir: Atazanavir absorption may be impaired based on known interactions with other agents that increase gastric pH. Use with caution. See atazanavir label for specific recommendations.

Delavirdine: Delavirdine absorption may be impaired based on known interactions with other agents that increase gastric pH. Chronic use of H2-receptor antagonists with delavirdine is not recommended.

Gefitinib: Gefitinib exposure was reduced by 44% with the coadministration of ranitidine and sodium bicarbonate (dosed to maintain gastric pH above 5.0). Use with caution.

Glipizide: In diabetic patients, glipizide exposure was increased by 34% following a single 150-mg dose of oral ranitidine. Use appropriate clinical monitoring when initiating or discontinuing ranitidine.

Ketoconazole: Oral ketoconazole exposure was reduced by up to 95% when oral ranitidine was coadministered in a regimen to maintain a gastric pH of 6 or above. The degree of interaction with usual dose of ranitidine (150 mg twice daily) is unknown.

Midazolam: Oral midazolam exposure in 5 healthy volunteers was increased by up to 65% when administered with oral ranitidine at a dose of 150 mg twice daily. However, in another interaction study in 8 volunteers receiving IV midazolam, a 300 mg oral dose of ranitidine increased midazolam exposure by about 9%. Monitor patients for excessive or prolonged sedation when ranitidine is coadministered with oral midazolam.

Triazolam: Triazolam exposure in healthy volunteers was increased by approximately 30% when administered with oral ranitidine at a dose of 150 mg twice daily. Monitor patients for excessive or prolonged sedation.

Carcinogenesis, Mutagenesis, Impairment of Fertility

There was no indication of tumorigenic or carcinogenic effects in life-span studies in mice and rats at oral dosages up to 2,000 mg/kg/day.

Ranitidine was not mutagenic in standard bacterial tests (Salmonella, Escherichia coli) for mutagenicity at concentrations up to the maximum recommended for these assays.

In a dominant lethal assay, a single oral dose of 1,000 mg/kg to male rats was without effect on the outcome of 2 matings per week for the next 9 weeks.

Pregnancy

Teratogenic Effects: Pregnancy Category B. Reproduction studies have been performed in rats and rabbits at oral doses up to 160 times the human oral dose and have revealed no evidence of impaired fertility or harm to the fetus due to ranitidine. There are, however, no adequate and well-controlled studies in pregnant women. Because animal reproduction studies are not always predictive of human response, this drug should be used during pregnancy only if clearly needed.

Nursing Mothers

Ranitidine is secreted in human milk. Caution should be exercised when ZANTAC is administered to a nursing mother.

Pediatric Use

The safety and effectiveness of ZANTAC Injection have been established in the age-group of 1 month to 16 years for the treatment of duodenal ulcer. Use of ZANTAC in this age-group is supported by adequate and well-controlled studies in adults, as well as additional pharmacokinetic data in pediatric patients, and an analysis of the published literature.

Safety and effectiveness in pediatric patients for the treatment of pathological hypersecretory conditions have not been established.

Limited data in neonatal patients (less than 1 month of age) receiving ECMO suggest that ZANTAC may be useful and safe for increasing gastric pH for patients at risk of gastrointestinal hemorrhage.

Geriatric Use

Clinical studies of ZANTAC Injection did not include sufficient numbers of subjects aged 65 and over to determine whether they responded differently from younger subjects. However, in clinical studies of oral formulations of ZANTAC, of the total number of subjects enrolled in US and foreign controlled clinical trials, for which there were subgroup analyses, 4,197 were 65 and over, while 899 were 75 and over. No overall differences in safety or effectiveness were observed between these subjects and younger subjects, and other reported clinical experience has not identified differences in responses between the elderly and younger patients, but greater sensitivity of some older individuals cannot be ruled out.

This drug is known to be substantially excreted by the kidney and the risk of toxic reactions to this drug may be greater in patients with impaired renal function. Because elderly patients are more likely to have decreased renal function, caution should be exercised in dose selection, and it may be useful to monitor renal function (see CLINICAL PHARMACOLOGY: Pharmacokinetics: Geriatric Use and DOSAGE AND ADMINISTRATION: Dosage Adjustment for Patients With Impaired Renal Function).

ADVERSE REACTIONS

Transient pain at the site of IM injection has been reported. Transient local burning or itching has been reported with IV administration of ZANTAC.

The following have been reported as events in clinical trials or in the routine management of patients treated with oral or parenteral ZANTAC. The relationship to therapy with ZANTAC has been unclear in many cases. Headache, sometimes severe, seems to be related to administration of ZANTAC.

Central Nervous System

Rarely, malaise, dizziness, somnolence, insomnia, and vertigo. Rare cases of reversible mental confusion, agitation, depression, and hallucinations have been reported, predominantly in severely ill elderly patients. Rare cases of reversible blurred vision suggestive of a change in accommodation have been reported. Rare reports of reversible involuntary motor disturbances have been received.

Cardiovascular

As with other H2-blockers, rare reports of arrhythmias such as tachycardia, bradycardia, asystole, atrioventricular block, and premature ventricular beats.

Gastrointestinal

Constipation, diarrhea, nausea/vomiting, abdominal discomfort/pain, and rare reports of pancreatitis.

Hepatic

In normal volunteers, SGPT values were increased to at least twice the pretreatment levels in 6 of 12 subjects receiving 100 mg intravenously 4 times daily for 7 days, and in 4 of 24 subjects receiving 50 mg intravenously 4 times daily for 5 days. There have been occasional reports of hepatocellular, cholestatic, or mixed hepatitis, with or without jaundice. In such circumstances, ranitidine should be immediately discontinued. These events are usually reversible, but in rare circumstances death has occurred. Rare cases of hepatic failure have also been reported.

Musculoskeletal

Rare reports of arthralgias and myalgias.

Hematologic

Blood count changes (leukopenia, granulocytopenia, and thrombocytopenia) have occurred in a few patients. These were usually reversible. Rare cases of agranulocytosis, pancytopenia, sometimes with marrow hypoplasia, and aplastic anemia and exceedingly rare cases of acquired immune hemolytic anemia have been reported.

Endocrine

Controlled studies in animals and humans have shown no stimulation of any pituitary hormone by ZANTAC and no antiandrogenic activity, and cimetidine-induced gynecomastia and impotence in hypersecretory patients have resolved when ZANTAC has been substituted. However, occasional cases of impotence and loss of libido have been reported in male patients receiving ZANTAC, but the incidence did not differ from that in the general population. Rare cases of breast symptoms and conditions, including galactorrhea and gynecomastia, have been reported in both males and females.

Integumentary

Rash, including rare cases of erythema multiforme. Rare cases of alopecia and vasculitis.

Respiratory

A large epidemiological study suggested an increased risk of developing pneumonia in current users of histamine-2–receptor antagonists (H2RAs) compared to patients who had stopped H2RA treatment, with an observed adjusted relative risk of 1.63 (95% CI, 1.07–2.48). However, a causal relationship between use of H2RAs and pneumonia has not been established.

Other

Rare cases of hypersensitivity reactions (e.g., bronchospasm, fever, rash, eosinophilia), anaphylaxis, angioneurotic edema, acute interstitial nephritis, and small increases in serum creatinine.

To report SUSPECTED ADVERSE REACTIONS, contact Teligent Pharma, Inc. at 1-856-697-1441, or FDA at 1-800-FDA-1088 or www.fda.gov/medwatch.

OVERDOSAGE

There has been virtually no experience with overdosage with ZANTAC Injection and limited experience with oral doses of ranitidine. Reported acute ingestions of up to 18 g orally have been associated with transient adverse effects similar to those encountered in normal clinical experience (see ADVERSE REACTIONS). In addition, abnormalities of gait and hypotension have been reported.

When overdosage occurs, clinical monitoring and supportive therapy should be employed.

Studies in dogs receiving dosages of ZANTAC in excess of 225 mg/kg/day have shown muscular tremors, vomiting, and rapid respiration. Single oral doses of 1,000 mg/kg in mice and rats were not lethal. Intravenous LD50 values in mice and rats were 77 and 83 mg/kg, respectively.

DOSAGE AND ADMINISTRATION

Parenteral Administration

In some hospitalized patients with pathological hypersecretory conditions or intractable duodenal ulcers, or in patients who are unable to take oral medication, ZANTAC may be administered parenterally according to the following recommendations:

Intramuscular Injection: 50 mg (2 mL) every 6 to 8 hours. (No dilution necessary.)

Intermittent Intravenous Injection:

a. Intermittent Bolus: 50 mg (2 mL) every 6 to 8 hours. Dilute ZANTAC Injection, 50 mg, in 0.9% sodium chloride injection or other compatible IV solution (see Stability) to a concentration no greater than 2.5 mg/mL (20 mL). Inject at a rate no greater than 4 mL/min (5 minutes).

b. Intermittent Infusion: 50 mg (2 mL) every 6 to 8 hours. Dilute ZANTAC Injection, 50 mg, in 5% dextrose injection or other compatible IV solution (see Stability) to a concentration no greater than 0.5 mg/mL (100 mL). Infuse at a rate no greater than 5 to 7 mL/min (15 to 20 minutes).

In some patients it may be necessary to increase dosage. When this is necessary, the increases should be made by more frequent administration of the dose, but generally should not exceed 400 mg/day.

Continuous Intravenous Infusion: Add ZANTAC Injection to 5% dextrose injection or other compatible IV solution (see Stability). Deliver at a rate of 6.25 mg/hour (e.g., 150 mg [6 mL] of ZANTAC Injection in 250 mL of 5% dextrose injection at 10.7 mL/hour).

For Zollinger-Ellison patients, dilute ZANTAC Injection in 5% dextrose injection or other compatible IV solution (see Stability) to a concentration no greater than 2.5 mg/mL. Start the infusion at a rate of 1.0 mg/kg/hour. If after 4 hours either a measured gastric acid output is >10 mEq/hour or the patient becomes symptomatic, the dose should be adjusted upward in 0.5-mg/kg/hour increments, and the acid output should be remeasured. Dosages up to 2.5 mg/kg/hour and infusion rates as high as 220 mg/hour have been used.

Pediatric Use

While limited data exist on the administration of IV ranitidine to children, the recommended dose in pediatric patients is for a total daily dose of 2 to 4 mg/kg, to be divided and administered every 6 to 8 hours, up to a maximum of 50 mg given every 6 to 8 hours. This recommendation is derived from adult clinical studies and pharmacokinetic data in pediatric patients. Limited data in neonatal patients (less than 1 month of age) receiving ECMO have shown that a dose of 2 mg/kg is usually sufficient to increase gastric pH to >4 for at least 15 hours. Therefore, doses of 2 mg/kg given every 12 to 24 hours or as a continuous infusion should be considered.

Dosage Adjustment for Patients With Impaired Renal Function

The administration of ranitidine as a continuous infusion has not been evaluated in patients with impaired renal function. On the basis of experience with a group of subjects with severely impaired renal function treated with ZANTAC, the recommended dosage in patients with a creatinine clearance <50 mL/min is 50 mg every 18 to 24 hours. Should the patient's condition require, the frequency of dosing may be increased to every 12 hours or even further with caution. Hemodialysis reduces the level of circulating ranitidine. Ideally, the dosing schedule should be adjusted so that the timing of a scheduled dose coincides with the end of hemodialysis.

Elderly patients are more likely to have decreased renal function, therefore caution should be exercised in dose selection, and it may be useful to monitor renal function (see CLINICAL PHARMACOLOGY: Pharmacokinetics: Geriatric Use and PRECAUTIONS: Geriatric Use).

Stability

Undiluted, ZANTAC Injection tends to exhibit a yellow color that may intensify over time without adversely affecting potency. ZANTAC Injection is stable for 48 hours at room temperature when added to or diluted with most commonly used IV solutions, e.g., 0.9% sodium chloride injection, 5% dextrose injection, 10% dextrose injection, lactated ringer's injection, or 5% sodium bicarbonate injection.

ZANTAC Injection Premixed in flexible plastic containers is sterile through the expiration date on the label when stored under recommended conditions.

Note: Parenteral drug products should be inspected visually for particulate matter and discoloration before administration whenever solution and container permit.

HOW SUPPLIED

ZANTAC® Injection, 25 mg/mL, containing phenol 0.5% as preservative, is available as follows:

NDC 52565-101-25, 2 mL single-dose vials (Carton of 25)

NDC 52565-102-05, 6 mL multidose vials (Carton of 5)

Store between 4° and 25°C (39° and 77°F); excursions permitted to 30°C (86°F). Protect from light.

Exposure of pharmaceutical products to heat should be minimized. Avoid excessive heat; however, brief exposure up to 40°C does not adversely affect the product. Protect from freezing.

Manufactured by:
Teligent Pharma, Inc.
Buena, NJ 08310

ZANTAC® is a registered trademark of Boehringer Ingelheim Pharmaceuticals, Inc., used under license.

MULTISTIX® is a registered trademark of Bayer Healthcare LLC.

PI-ZAN-00
Rev 04/2019

PACKAGE LABEL.PRINCIPAL DISPLAY PANEL - 2 mL Single-Dose Vial

NDC 52565-101-01
Zantac® (ranitidine) Injection
50 mg/2 mL
(25 mg/mL)
FOR IV, IM OR IV USE
2 mL Single Dose Vial
Sterile Rx only
Contains 0.5% phenol as a preservative.
Manufactured by:
Teligent Pharma, Inc.
Buena, NJ 08310
C101195
CL-101-00 Rev 04/2019

PACKAGE LABEL.PRINCIPAL DISPLAY PANEL - 6-mL Multi-Dose Vial

NDC 52565-102-01
Zantac® (ranitidine) Injection
150 mg/6 mL (25 mg/mL*)
For IV or IM injection, or IV infusion
6 mL Multiple Dose Vial
Sterile
Rx only